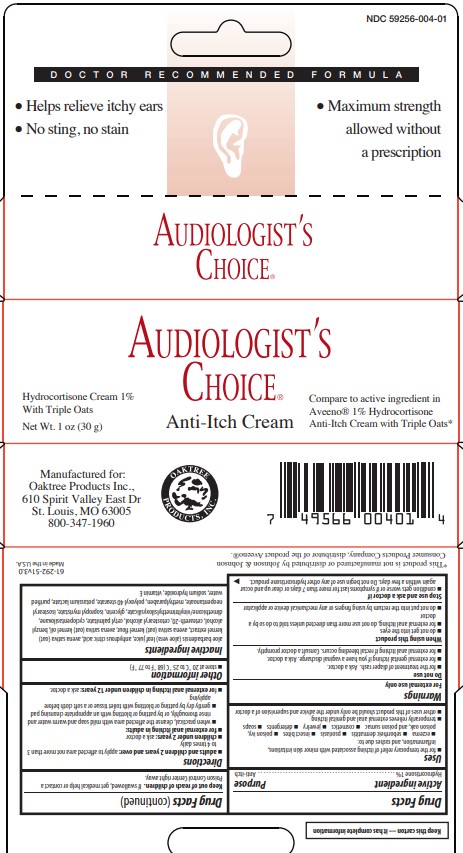 DRUG LABEL: Audiologist Anti-itch
NDC: 59256-004 | Form: CREAM
Manufacturer: OAKTREE PRODUCTS, INC.
Category: otc | Type: HUMAN OTC DRUG LABEL
Date: 20241213

ACTIVE INGREDIENTS: HYDROCORTISONE 1 g/100 g
INACTIVE INGREDIENTS: PETROLATUM; CETOSTEARYL ALCOHOL; GLYCERIN; PROPYLPARABEN; ALOE VERA LEAF; SODIUM LAURYL SULFATE; LIGHT MINERAL OIL; METHYLPARABEN; WATER; WHITE WAX; SODIUM CETOSTEARYL SULFATE

Audiologist Hydrocortisone 1 oz

Active Ingredient

Hydrocortisone 1 %

Uses

for the temporary relief of itching associated with minor skin irritations, inflammation, and rashes due to:

eczema

seborrheic dermatitis

psoriasis

insect bites

poison ivy, poison oak, and poison sumac

cosmetics

jewelry

detergents

soaps

temporarily relieves external anal and genital itching

other uses of this product should be only under the advice and supervision of a doctor

Warnings

For external use only

When using this product

do not get into the eyes

for external anal itching, do not use more than directed unless told to do so by a doctor

do not put into the rectum by using fingers or any mechanical device or applicator

Do not use

for the treatment of diaper rash. Ask a doctor.

for external genital itching if you have a vaginal discharge. Ask a doctor.

for external anal itching if rectal bleeding occurs. Consult a doctor promptly.

Stop us and ask doctor if

condition gets worse, or if symptoms last for more than 7 days or clear up and occur again within a few days. Do not begin use of any other hydrocortisone product.

Keep out of reach of children

If swallowed, get medical help or contact a Poison Control Center right away.

Directions

adults and children 2 years and over: apply to affected area not more than 3 to 4 times daily

children under 2 years: ask a doctor

for external anal itching in adults:

when practical, cleanse the affected area with mild soap and warm water and rinse thoroughly, or by patting or blotting with an appropriate cleansing pad.

gently dry by patting or blotting with toilet tissue or a soft cloth before applying.

for external anal itching in children under 12 years: ask a doctor

Other information

store at 20 °C to 25 °C (68 °F to 77 °F)

Inactive ingredient

aloe barbadensis (aloe vera) leaf juice, cetearyl alcohol, glycerin, methylparaben, mineral oil, propylparaben, purified water, sodium cetearyl sulfate, sodium lauryl sulfate, white petrolatum, white wax

Purpose

Anti-Itch